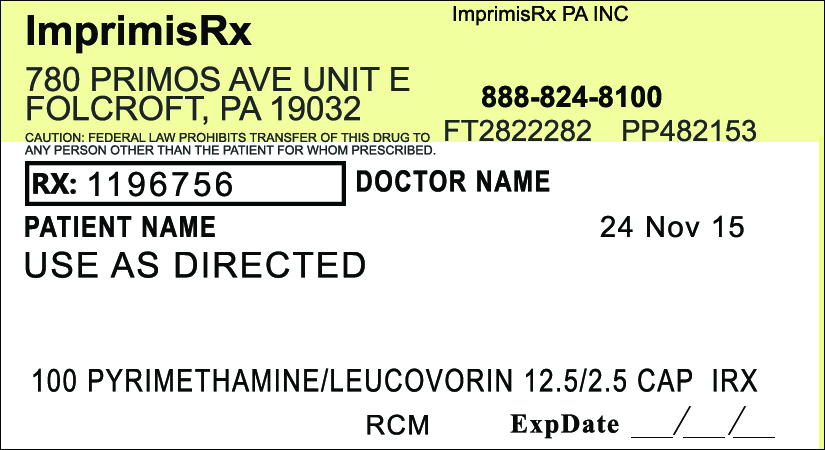 DRUG LABEL: Pyrimethamine Leucovorin
NDC: 70271-430 | Form: CAPSULE
Manufacturer: ImprimisRx PA, Inc. d/b/a ImprimisRx
Category: prescription | Type: HUMAN PRESCRIPTION DRUG LABEL
Date: 20151127

ACTIVE INGREDIENTS: PYRIMETHAMINE 12.5 mg/1 1; LEUCOVORIN CALCIUM 2.5 mg/1 1
INACTIVE INGREDIENTS: CELLULOSE, MICROCRYSTALLINE 100 mg/1 1

Pyrimethamine Leucovorin (12.5mg-2.5mg)